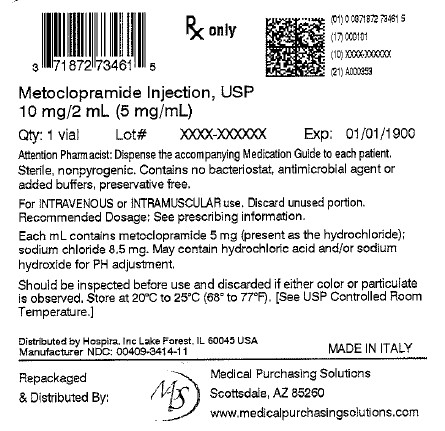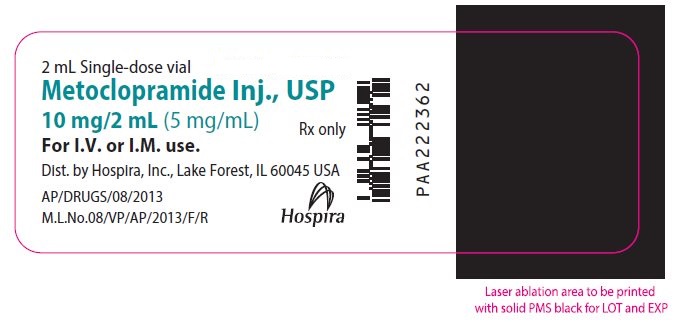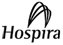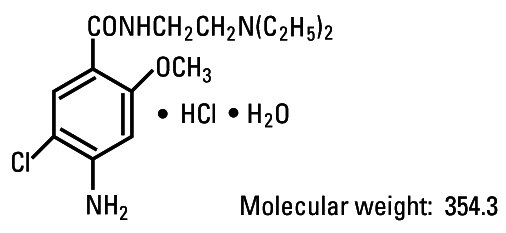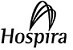 DRUG LABEL: Metoclopramide
NDC: 71872-7346 | Form: INJECTION, SOLUTION
Manufacturer: Medical Purchasing Solutions, LLC.
Category: prescription | Type: HUMAN PRESCRIPTION DRUG LABEL
Date: 20251023

ACTIVE INGREDIENTS: METOCLOPRAMIDE HYDROCHLORIDE 5 mg/1 mL
INACTIVE INGREDIENTS: SODIUM CHLORIDE 8.5 mg/1 mL; HYDROCHLORIC ACID; SODIUM HYDROXIDE; WATER

Metoclopramide

Injection, USP
Fliptop Vial

Rx only

WARNING: TARDIVE DYSKINESIA

Treatment with metoclopramide can cause tardive dyskinesia, a serious movement disorder that is often irreversible. The risk of developing tardive dyskinesia increases with duration of treatment and total cumulative dose.

Metoclopramide therapy should be discontinued in patients who develop signs or symptoms of tardive dyskinesia. There is no known treatment for tardive dyskinesia. In some patients, symptoms may lessen or resolve after metoclopramide treatment is stopped.

Treatment with metoclopramide for longer than 12 weeks should be avoided in all but rare cases where therapeutic benefit is thought to outweigh the risk of developing tardive dyskinesia (see WARNINGS).

DESCRIPTION

Metoclopramide hydrochloride is a white or practically white, crystalline, odorless or practically odorless powder. It is very soluble in water, freely soluble in alcohol, sparingly soluble in chloroform, practically insoluble in ether. Chemically it is 4-amino-5-chloro-N-[2-(diethylamino)ethyl]-2-methoxybenzamide monohydrochloride monohydrate. It has the following structural formula:

Molecular formula: C14H22ClN3O2• HCl • H2O

Metoclopramide Injection, USP is a sterile, nonpyrogenic solution of metoclopramide hydrochloride in water for injection. Each milliliter contains metoclopramide base 5 mg (as the hydrochloride monohydrate); 8.5 mg sodium chloride. May contain hydrochloric acid and/or sodium hydroxide for pH adjustment; pH 4.4 (2.5 to 6.5).

The solution contains no bacteriostat, antimicrobial agent or added buffer and is intended for use only as a single-dose injection. When smaller doses are required, the unused portion should be discarded.

This product is light sensitive. It should be inspected before use and discarded if either color or particulate is observed.

Metoclopramide Injection is intended for intravenous or intramuscular administration.

CLINICAL PHARMACOLOGY

Metoclopramide stimulates motility of the upper gastrointestinal tract without stimulating gastric, biliary, or pancreatic secretions. Its mode of action is unclear. It seems to sensitize tissues to the action of acetylcholine. The effect of metoclopramide on motility is not dependent on intact vagal innervation, but it can be abolished by anticholinergic drugs.

Metoclopramide increases the tone and amplitude of gastric (especially antral) contractions, relaxes the pyloric sphincter and the duodenal bulb, and increases peristalsis of the duodenum and jejunum resulting in accelerated gastric emptying and intestinal transit. It increases the resting tone of the lower esophageal sphincter. It has little, if any, effect on the motility of the colon or gallbladder.

In patients with gastroesophageal reflux and low LESP (lower esophageal sphincter pressure), single oral doses of metoclopramide produce dose-related increases in LESP. Effects begin at about 5 mg and increase through 20 mg (the largest dose tested). The increase in LESP from a 5 mg dose lasts about 45 minutes and that of 20 mg lasts between 2 and 3 hours. Increased rate of stomach emptying has been observed with single oral doses of 10 mg.

The antiemetic properties of metoclopramide appear to be a result of its antagonism of central and peripheral dopamine receptors. Dopamine produces nausea and vomiting by stimulation of the medullary chemoreceptor trigger zone (CTZ), and metoclopramide blocks stimulation of the CTZ by agents like l-dopa or apomorphine which are known to increase dopamine levels or to possess dopamine-like effects. Metoclopramide also abolishes the slowing of gastric emptying caused by apomorphine.

Like the phenothiazines and related drugs, which are also dopamine antagonists, metoclopramide produces sedation and may produce extrapyramidal reactions, although these are comparatively rare (see WARNINGS). Metoclopramide inhibits the central and peripheral effects of apomorphine, induces release of prolactin and causes a transient increase in circulating aldosterone levels, which may be associated with transient fluid retention.

The onset of pharmacological action of metoclopramide is 1 to 3 minutes following an intravenous dose, 10 to 15 minutes following intramuscular administration, and 30 to 60 minutes following an oral dose, pharmacological effects persist for 1 to 2 hours.

Pharmacokinetics

Metoclopramide is rapidly and well absorbed. Relative to an intravenous dose of 20 mg, the absolute oral bioavailability of metoclopramide is 80% ± 15.5% as demonstrated in a crossover study of 18 subjects. Peak plasma concentrations occur at about 1 to 2 hours after a single oral dose. Similar time to peak is observed after individual doses at steady state.

In a single-dose study of 12 subjects, the area under the drug concentration-time curve increases linearly with doses from 20 to 100 mg. Peak concentrations increase linearly with dose; time to peak concentrations remains the same; whole body clearance is unchanged; and the elimination rate remains the same. The average elimination half-life in individuals with normal renal function is 5 to 6 hours. Linear kinetic processes adequately describe the absorption and elimination of metoclopramide.

Approximately 85% of the radioactivity of an orally administered dose appears in the urine within 72 hours. Of the 85% eliminated in the urine, about half is present as free or conjugated metoclopramide.

The drug is not extensively bound to plasma proteins (about 30%). The whole body volume of distribution is high (about 3.5 L/kg) which suggests extensive distribution of drug to the tissues.

Renal impairment affects the clearance of metoclopramide. In a study with patients with varying degrees of renal impairment, a reduction in creatinine clearance was correlated with a reduction in plasma clearance, renal clearance, non-renal clearance, and increase in elimination half-life. The kinetics of metoclopramide in the presence of renal impairment remained linear however. The reduction in clearance as a result of renal impairment suggests that adjustment downward of maintenance dosage should be done to avoid drug accumulation.

Adult Pharmacokinetic Data
Parameter | Value
Vd (L/kg) | ~3.5
Plasma Protein Binding | ~30%
t1/2(hr) | 5 to 6
Oral Bioavailability | 80% ± 15.5%

In pediatric patients, the pharmacodynamics of metoclopramide following oral and intravenous administration are highly variable and a concentration-effect relationship has not been established.

There are insufficient reliable data to conclude whether the pharmacokinetics of metoclopramide in adults and the pediatric population are similar. Although there are insufficient data to support the efficacy of metoclopramide in pediatric patients with symptomatic gastroesophageal reflux (GER) or cancer chemotherapy-related nausea and vomiting, its pharmacokinetics have been studied in these patient populations.

In an open-label study, six pediatric patients (age range, 3.5 weeks to 5.4 months) with GER received metoclopramide 0.15 mg/kg oral solution every 6 hours for 10 doses. The mean peak plasma concentration of metoclopramide after the tenth dose was 2-fold (56.8 mcg/L) higher compared to that observed after the first dose (29 mcg/L) indicating drug accumulation with repeated dosing. After the tenth dose, the mean time to reach peak concentrations (2.2 hrs), half-life (4.1 hrs), clearance (0.67 L/h/kg), and volume of distribution (4.4 L/kg) of metoclopramide were similar to those observed after the first dose. In the youngest patient (age, 3.5 weeks), metoclopramide half-life after the first and the tenth dose (23.1 and 10.3 hrs, respectively) was significantly longer compared to other infants due to reduced clearance. This may be attributed to immature hepatic and renal systems at birth.

Single intravenous doses of metoclopramide 0.22 to 0.46 mg/kg (mean, 0.35 mg/kg) were administered over 5 minutes to nine pediatric cancer patients receiving chemotherapy (mean age, 11.7 years; range, 7 to 14 yrs) for prophylaxis of cytotoxic-induced vomiting. The metoclopramide plasma concentrations extrapolated to time zero ranged from 65 to 395 mcg/L (mean, 152 mcg/L). The mean elimination half-life, clearance, and volume of distribution of metoclopramide were 4.4 hrs (range, 1.7 to 8.3 hrs), 0.56 L/h/kg (range, 0.12 to 1.20 L/h/kg), and 3.0 L/kg (range, 1.0 to 4.8 L/kg), respectively.

In another study, nine pediatric cancer patients (age range, 1 to 9 yrs) received 4 to 5 intravenous infusions (over 30 minutes) of metoclopramide at a dose of 2 mg/kg to control emesis. After the last dose, the peak serum concentrations of metoclopramide ranged from 1060 to 5680 mcg/L. The mean elimination half-life, clearance, and volume of distribution of metoclopramide were 4.5 hrs (range, 2.0 to 12.5 hrs), 0.37 L/h/kg (range, 0.10 to 1.24 L/h/kg), and 1.93 L/kg (range, 0.95 to 5.50 L/kg), respectively.

Pediatric Pharmacokinetic Studies
Reference | Dose, Route | t1/2; (hr) | CI; (L/hr/kg) | Vd; (L/kg) | Cmax; (mcg/L)
1. | 0.35 mg/kg; IV over 5 min | 4.4 ± 0.56 | 0.56 ± 0.10 | 3.0 ± 0.38; (Dose/Cp^0) | 152 ± 31
2. | 2 mg/kg; 30 min IV infusion; 4 to 5 times within; 9.5 hours | 4.5a | 0.37a | 1.93a | 1060 to 5680a
a SEM not available.
1. Bateman, DN, et al. Br J Clin Pharmac15 :557-559, 1983.
2. Ford, C. Clin Pharmac Ther43:196, 1988.

INDICATIONS AND USAGE

Diabetic Gastroparesis (Diabetic Gastric Stasis)

Metoclopramide is indicated for the relief of symptoms associated with acute and recurrent diabetic gastric stasis.

The Prevention of Nausea and Vomiting Associated with Emetogenic Cancer Chemotherapy

Metoclopramide Injection, USP is indicated for the prophylaxis of vomiting associated with emetogenic cancer chemotherapy.

The Prevention of Postoperative Nausea and Vomiting

Metoclopramide Injection, USP is indicated for the prophylaxis of postoperative nausea and vomiting in those circumstances where nasogastric suction is undesirable.

Small Bowel Intubation

Metoclopramide Injection, USP may be used to facilitate small bowel intubation in adults and pediatric patients in whom the tube does not pass the pylorus with conventional maneuvers.

Radiological Examination

Metoclopramide Injection, USP may be used to stimulate gastric emptying and intestinal transit of barium in cases where delayed emptying interferes with radiological examination of the stomach and/or small intestine.

CONTRAINDICATIONS

Metoclopramide should not be used whenever stimulation of gastrointestinal motility might be dangerous, e.g., in the presence of gastrointestinal hemorrhage, mechanical obstruction or perforation.

Metoclopramide is contraindicated in patients with pheochromocytoma because the drug may cause a hypertensive crisis, probably due to release of catecholamines from the tumor. Such hypertensive crises may be controlled by phentolamine.

Metoclopramide is contraindicated in patients with known sensitivity or intolerance to the drug.

Metoclopramide should not be used in epileptics or patients receiving other drugs which are likely to cause extrapyramidal reactions, since the frequency and severity of seizures or extrapyramidal reactions may be increased.

WARNINGS

Neuroleptic Malignant Syndrome (NMS)

There have been rare reports of an uncommon but potentially fatal symptom complex sometimes referred to as Neuroleptic Malignant Syndrome (NMS) associated with metoclopramide. Clinical manifestations of NMS include hyperthermia, muscle rigidity, altered consciousness, and evidence of autonomic instability (irregular pulse or blood pressure, tachycardia, diaphoresis and cardiac arrhythmias).

The diagnostic evaluation of patients with this syndrome is complicated. In arriving at a diagnosis, it is important to identify cases where the clinical presentation includes both serious medical illness (e.g., pneumonia, systemic infection, etc.) and untreated or inadequately treated extrapyramidal signs and symptoms (EPS). Other important considerations in the differential diagnosis include central anticholinergic toxicity, heat stroke, malignant hyperthermia, drug fever and primary central nervous system (CNS) pathology.

The management of NMS should include 1) immediate discontinuation of metoclopramide and other drugs not essential to concurrent therapy, 2) intensive symptomatic treatment and medical monitoring, and 3) treatment of any concomitant serious medical problems for which specific treatments are available. Bromocriptine and dantrolene sodium have been used in treatment of NMS, but their effectiveness have not been established (see ADVERSE REACTIONS).

Extrapyramidal Symptoms (EPS)

Acute Dystonic Reactions

Acute dystonic reactions occur in approximately 1 in 500 patients treated with the usual adult dosages of 30 to 40 mg/day of metoclopramide. These usually are seen during the first 24 to 48 hours of treatment with metoclopramide, occur more frequently in pediatric patients and adult patients less than 30 years of age and are even more frequent at the higher doses used in prophylaxis of vomiting due to cancer chemotherapy. These symptoms may include involuntary movements of limbs and facial grimacing, torticollis, oculogyric crisis, rhythmic protrusion of tongue, bulbar type of speech, trismus, or dystonic reactions resembling tetanus. Rarely, dystonic reactions may present as stridor and dyspnea, possibly due to laryngospasm. If these symptoms should occur, inject 50 mg Benadryl®(diphenhydramine hydrochloride) intramuscularly, and they usually will subside. Cogentin®(benztropine mesylate), 1 to 2 mg intramuscularly, may also be used to reverse these reactions.

Tardive Dyskinesia (see Boxed Warnings)

Treatment with metoclopramide can cause tardive dyskinesia (TD), a potentially irreversible and disfiguring disorder characterized by involuntary movements of the face, tongue, or extremities. The risk of tardive dyskinesia increases with the duration of treatment and the total cumulative dose. An analysis of utilization patterns showed that about 20% of patients who used metoclopramide took it longer than 12 weeks. Treatment with metoclopramide for longer than the recommended 12 weeks should be avoided in all but rare cases where therapeutic benefit is thought to outweigh the risk of developing TD.

Although the risk of developing TD in the general population may be increased among the elderly, women, and diabetics, it is not possible to predict which patients will develop metoclopramide-induced TD. Both the risk of developing TD and the likelihood that TD will become irreversible increase with duration of treatment and total cumulative dose.

Metoclopramide should be discontinued in patients who develop signs or symptoms of TD. There is no known effective treatment for established cases of TD, although in some patients, TD may remit, partially or completely, within several weeks to months after metoclopramide is withdrawn.

Metoclopramide itself may suppress, or partially suppress, the signs of TD, thereby masking the underlying disease process. The effect of this symptomatic suppression upon the long-term course of TD is unknown. Therefore, metoclopramide should not be used for the symptomatic control of TD.

Parkinsonian-like symptoms, including bradykinesia, tremor, cogwheel rigidity, or mask-like facies, have occurred, more commonly within the first 6 months after beginning treatment with metoclopramide, but occasionally after longer periods. These symptoms generally subside within 2 to 3 months following discontinuance of metoclopramide. Patients with pre-existing Parkinson's disease should be given metoclopramide cautiously, if at all, since such patients may experience exacerbation of parkinsonian symptoms when taking metoclopramide.

Depression

Mental depression has occurred in patients with and without prior history of depression. Symptoms have ranged from mild to severe and have included suicidal ideation and suicide. Metoclopramide should be given to patients with a prior history of depression only if the expected benefits outweigh the potential risks.

PRECAUTIONS

General

In one study in hypertensive patients, intravenously administered metoclopramide was shown to release catecholamines, hence, caution should be exercised when metoclopramide is used in patients with hypertension.

Intravenous injections of undiluted metoclopramide should be made slowly allowing 1 to 2 minutes for 10 mg since a transient but intense feeling of anxiety and restlessness, followed by drowsiness, may occur with rapid administration.

Because metoclopramide produces a transient increase in plasma aldosterone, certain patients, especially those with cirrhosis or congestive heart failure, may be at risk of developing fluid retention and volume overload. If these side effects occur at any time during metoclopramide therapy, the drug should be discontinued.

Intravenous administration of Metoclopramide Injection, USP, diluted in a parenteral solution should be made slowly over a period of not less than 15 minutes.

Giving a promotility drug such as metoclopramide theoretically could put increased pressure on suture lines following a gut anastomosis or closure. This possibility should be considered and weighed when deciding whether to use metoclopramide or nasogastric suction in the prevention of postoperative nausea and vomiting.

Information for Patients

A patient Medication Guide is available for metoclopramide. The prescriber or health professional should instruct patients, their families, and their caregivers to read the Medication Guide and should assist them in understanding its contents. Patients should be given the opportunity to discuss the contents of the Medication Guide and to obtain answers to any questions they may have. Refer to the accompanying Medication Guide.

Metoclopramide may impair the mental and/or physical abilities required for the performance of hazardous tasks such as operating machinery or driving a motor vehicle. The ambulatory patient should be cautioned accordingly.

Drug Interactions

The effects of metoclopramide on gastrointestinal motility are antagonized by anticholinergic drugs and narcotic analgesics. Additive sedative effects can occur when metoclopramide is given with alcohol, sedatives, hypnotics, narcotics or tranquilizers.

The finding that metoclopramide releases catecholamines in patients with essential hypertension suggests that it should be used cautiously, if at all, in patients receiving monoamine oxidase inhibitors.

Absorption of drugs from the stomach may be diminished (e.g., digoxin) by metoclopramide, whereas the rate and/or extent of absorption of drugs from the small bowel may be increased (e.g., acetaminophen, tetracycline, levodopa, ethanol, cyclosporine).

Gastroparesis (gastric stasis) may be responsible for poor diabetic control in some patients. Exogenously administered insulin may begin to act before food has left the stomach and lead to hypoglycemia. Because the action of metoclopramide will influence the delivery of food to the intestines and thus the rate of absorption, insulin dosage or timing of dosage may require adjustment.

Carcinogenesis, Mutagenesis, Impairment of Fertility

A 77-week study was conducted in rats with oral doses up to about 40 times the maximum recommended human daily dose. Metoclopramide elevates prolactin levels and the elevation persists during chronic administration. Tissue culture experiments indicate that approximately one-third of human breast cancers are prolactin-dependent in vitro, a factor of potential importance if the prescription of metoclopramide is contemplated in a patient with previously detected breast cancer. Although disturbances such as galactorrhea, amenorrhea, gynecomastia, and impotence have been reported with prolactin-elevating drugs, the clinical significance of elevated serum prolactin levels is unknown for most patients. An increase in mammary neoplasms has been found in rodents after chronic administration of prolactin-stimulating neuroleptic drugs and metoclopramide. Neither clinical studies nor epidemiologic studies conducted to date, however, have shown an association between chronic administration of these drugs and mammary tumorigenesis; the available evidence is too limited to be conclusive at this time.

An Ames mutagenicity test performed on metoclopramide was negative.

Pregnancy

Reproduction studies performed in rats, mice, and rabbits by the IM, IV, subcutaneous (SC), and oral routes at maximum levels ranging from 12 to 250 times the human dose have demonstrated no impairment of fertility or significant harm to the fetus due to metoclopramide. There are, however, no adequate and well-controlled studies in pregnant women. Because animal reproduction studies are not always predictive of human response, this drug should be used during pregnancy only if clearly needed.

Nursing Mothers

Metoclopramide is excreted in human milk. Caution should be exercised when metoclopramide is administered to a nursing mother.

Pediatric Use

Safety and effectiveness in pediatric patients have not been established except as stated to facilitate small bowel intubation (see OVERDOSAGEand DOSAGE AND ADMINISTRATION).

Care should be exercised in administering metoclopramide to neonates since prolonged clearance may produce excessive serum concentrations (see CLINICAL PHARMACOLOGY – Pharmacokinetics).

In addition, neonates have reduced levels of NADH-cytochrome b5reductase which, in combination with the aforementioned pharmacokinetic factors, make neonates more susceptible to methemoglobinemia (see OVERDOSAGE).

The safety profile of metoclopramide in adults cannot be extrapolated to pediatric patients. Dystonias and other extrapyramidal reactions associated with metoclopramide are more common in the pediatric population than in adults (see WARNINGSand ADVERSE REACTIONS – Extrapyramidal Reactions (EPS)).

Geriatric Use

Clinical studies of metoclopramide did not include sufficient numbers of subjects aged 65 and over to determine whether elderly subjects respond differently from younger subjects.

The risk of developing parkinsonian-like side effects increases with ascending dose. Geriatric patients should receive the lowest dose of metoclopramide that is effective. If parkinsonian-like symptoms develop in a geriatric patient receiving metoclopramide, metoclopramide should generally be discontinued before initiating any specific anti-parkinsonian agents (see WARNINGS).

The elderly may be at greater risk for tardive dyskinesia (see WARNINGS – Tardive Dyskinesia).

Sedation has been reported in metoclopramide users. Sedation may cause confusion and manifest as over-sedation in elderly (see CLINICAL PHARMACOLOGY, PRECAUTIONS – Information for Patientsand ADVERSE REACTIONS – CNS Effects).

Metoclopramide is known to be substantially excreted by the kidney, and the risk of toxic reactions to this drug may be greater in patients with impaired renal function (see DOSAGE AND ADMINISTRATION – Use in Patients with Renal or Hepatic Impairment).

For these reasons, dose selection for an elderly patient should be cautious, usually starting at the low end of the dosing range, reflecting the greater frequency of decreased renal function, concomitant disease, or other drug therapy in the elderly (see DOSAGE AND ADMINISTRATION – Use in Patients with Renal or Hepatic Impairment).

Other Special Populations

Patients with NADH-cytochrome b5reductase deficiency are at an increased risk of developing methemoglobinemia and/or sulfhemoglobinemia when metoclopramide is administered. In patients with G6PD deficiency who experience metoclopramide-induced methemoglobinemia, methylene blue treatment is not recommended (see OVERDOSAGE).

ADVERSE REACTIONS

In general, the incidence of adverse reactions correlates with the dose and duration of metoclopramide administration. The following reactions have been reported, although in most instances, data do not permit an estimate of frequency.

CNS Effects

Restlessness, drowsiness, fatigue and lassitude may occur in patients receiving the recommended prescribed dosage of metoclopramide injection. Insomnia, headache, confusion, dizziness, or mental depression with suicidal ideation also may occur (see WARNINGS). In cancer chemotherapy patients being treated with 1 to 2 mg/kg per dose, incidence of drowsiness is about 70%. There are isolated reports of convulsive seizures without a clear-cut relationship to metoclopramide. Rarely, hallucinations have been reported.

Extrapyramidal Reactions (EPS)

Acute dystonic reactions, the most common type of EPS associated with metoclopramide, occur in approximately 0.2% of patients (1 in 500) treated with 30 to 40 mg of metoclopramide per day. In cancer chemotherapy patients receiving 1 to 2 mg/kg per dose, the incidence is 2% in patients over the ages of 30 to 35, and 25% or higher in pediatric patients and adult patients less than 30 years of age who have not had prophylactic administration of diphenhydramine. Symptoms include involuntary movements of limbs, facial grimacing, torticollis, oculogyric crisis, rhythmic protrusion of tongue, bulbar type of speech, trismus, opisthotonus (tetanus-like reactions) and rarely, stridor and dyspnea, possibly due to laryngospasm; ordinarily these symptoms are readily reversed by diphenhydramine (see WARNINGS).

Parkinsonian-like symptoms may include bradykinesia, tremor, cogwheel rigidity, mask-like facies (see WARNINGS).

Tardive dyskinesia most frequently is characterized by involuntary movements of the tongue, face, mouth or jaw, and sometimes by involuntary movements of the trunk and/or extremities; movements may be choreoathetotic in appearance (see WARNINGS).

Motor restlessness (akathisia) may consist of feelings of anxiety, agitation, jitteriness, and insomnia, as well as inability to sit still, pacing, and foot tapping. These symptoms may disappear spontaneously or respond to a reduction in dosage.

Neuroleptic Malignant Syndrome

Rare occurrences of neuroleptic malignant syndrome (NMS) have been reported. This potentially fatal syndrome is comprised of the symptom complex of hyperthermia, muscular rigidity, altered consciousness, and autonomic instability (see WARNINGS).

Endocrine Disturbances

Galactorrhea, amenorrhea, gynecomastia, impotence secondary to hyperprolactinemia (see PRECAUTIONS). Fluid retention secondary to transient elevation of aldosterone (see CLINICAL PHARMACOLOGY).

Cardiovascular

Hypotension, hypertension, supraventricular tachycardia, bradycardia, fluid retention, acute congestive heart failure, and possible atrioventricular (AV) block (see CONTRAINDICATIONSand PRECAUTIONS).

Gastrointestinal

Nausea and bowel disturbances, primarily diarrhea.

Hepatic

Rarely, cases of hepatotoxicity, characterized by such findings as jaundice and altered liver function tests, when metoclopramide was administered with other drugs with known hepatotoxic potential.

Renal

Urinary frequency and incontinence.

Hematologic

A few cases of neutropenia, leukopenia, or agranulocytosis, generally without a clear-cut relationship to metoclopramide. Methemoglobinemia, in adults and especially with overdosage in neonates (see OVERDOSAGE). Sulfhemoglobinemia in adults.

Allergic Reactions

A few cases of rash, urticaria, or bronchospasm, especially in patients with a history of asthma. Rarely, angioneurotic edema, including glossal or laryngeal edema.

Miscellaneous

Visual disturbances, Porphyria.

Transient flushing of the face and upper body, without alterations in vital signs, following high doses intravenously.

OVERDOSAGE

Symptoms of overdosage may include drowsiness, disorientation and extrapyramidal reactions. Anticholinergic or antiparkinson drugs or antihistamines with anticholinergic properties may be helpful in controlling the extrapyramidal reactions. Symptoms are self-limiting and usually disappear within 24 hours.

Hemodialysis removes relatively little metoclopramide, probably because of the small amount of the drug in blood relative to tissues. Similarly, continuous ambulatory peritoneal dialysis does not remove significant amounts of drug. It is unlikely that dosage would need to be adjusted to compensate for losses through dialysis. Dialysis is not likely to be an effective method of drug removal in overdose situations.

Unintentional overdose due to misadministration has been reported in infants and children with the use of metoclopramide syrup. While there was no consistent pattern to the reports associated with these overdoses, events included seizures, extrapyramidal reactions and lethargy.

Methemoglobinemia has occurred in premature and full-term neonates who were given overdoses of metoclopramide (1 to 4 mg/kg/day orally, intramuscularly or intravenously for 1 to 3 or more days). Methemoglobinemia can be reversed by the intravenous administration of methylene blue. However, methylene blue may cause hemolytic anemia in patients with G6PD deficiency, which may be fatal (see PRECAUTIONS – Other Special Populations).

DOSAGE AND ADMINISTRATION

For the Relief of Symptoms Associated with Diabetic Gastroparesis (Diabetic Gastric Stasis)

If only the earliest manifestations of diabetic gastric stasis are present, oral administration of metoclopramide may be initiated. However, if severe symptoms are present, therapy should begin with metoclopramide injection (IM or IV). Doses of 10 mg may be administered slowly by the intravenous route over a 1 to 2 minute period.

Administration of Metoclopramide Injection, USP up to 10 days may be required before symptoms subside, at which time oral administration of metoclopramide may be instituted. The physician should make a thorough assessment of the risks and benefits prior to prescribing further metoclopramide treatment.

For the Prevention of Nausea and Vomiting Associated with Emetogenic Cancer Chemotherapy

Intravenous infusions should be made slowly over a period of not less than 15 minutes, 30 minutes before beginning cancer chemotherapy and repeated every 2 hours for two doses, then every 3 hours for three doses.

The initial two doses should be 2 mg/kg if highly emetogenic drugs such as cisplatin or dacarbazine are used alone or in combination. For less emetogenic regimens, 1 mg/kg per dose may be adequate.

For doses in excess of 10 mg, Metoclopramide Injection, USP should be diluted in 50 mL of a parenteral solution.

The preferred parenteral solution is Sodium Chloride Injection (normal saline), which when combined with Metoclopramide Injection, USP, can be stored frozen for up to 4 weeks. Metoclopramide Injection, USP is degraded when admixed and frozen with Dextrose-5% in Water. Metoclopramide Injection, USP diluted in Sodium Chloride Injection, Dextrose-5% in Water, Dextrose-5% in 0.45% Sodium Chloride, Ringer's Injection, or Lactated Ringer's Injection may be stored up to 48 hours (without freezing) after preparation if protected from light. All dilutions may be stored unprotected from light under normal light conditions up to 24 hours after preparation.

If acute dystonic reactions should occur, inject 50 mg Benadryl®(diphenhydramine hydrochloride) intramuscularly, and the symptoms usually will subside.

For the Prevention of Postoperative Nausea and Vomiting

Metoclopramide Injection, USP should be given intramuscularly near the end of surgery. The usual adult dose is 10 mg; however, doses of 20 mg may be used.

To Facilitate Small Bowel Intubation

If the tube has not passed the pylorus with conventional maneuvers in 10 minutes, a single dose (undiluted) may be administered slowly by the intravenous route over a 1 to 2 minute period.

The recommended single dose is: Pediatric patients above 14 years of age and adults – 10 mg metoclopramide base. Pediatric patients (6 to 14 years of age) – 2.5 to 5 mg metoclopramide base; (under 6 years of age) – 0.1 mg/kg metoclopramide base.

To Aid in Radiological Examinations

In patients where delayed gastric emptying interferes with radiological examination of the stomach and/or small intestine, a single dose may be administered slowly by the intravenous route over a 1 to 2 minute period.

For dosage, see intubation, above.

Use in Patients with Renal or Hepatic Impairment

Since metoclopramide is excreted principally through the kidneys, in those patients whose creatinine clearance is below 40 mL/min, therapy should be initiated at approximately one-half the recommended dosage. Depending upon clinical efficacy and safety considerations, the dosage may be increased or decreased as appropriate.

See OVERDOSAGEsection for information regarding dialysis.

Metoclopramide undergoes minimal hepatic metabolism, except for simple conjugation. Its safe use has been described in patients with advanced liver disease whose renal function was normal.

NOTE:Parenteral drug products should be inspected visually for particulate matter and discoloration prior to administration whenever solution and container permit.

ADMIXTURE COMPATIBILITIES

Metoclopramide Injection, USP is compatible for mixing and injection with the following dosage forms to the extent indicated below:

Physically and Chemically Compatible Up to 48 Hours

Cimetidine Hydrochloride (SK&F), Mannitol, USP (Hospira), Potassium Acetate, USP (Invenex), Potassium Phosphate, USP (Invenex).

Physically Compatible Up to 48 Hours

Ascorbic Acid, USP (Hospira), Benztropine Mesylate, USP (MS&D), Cytarabine, USP (Upjohn), Dexamethasone Sodium Phosphate, USP (ESI, MS&D), Diphenhydramine Hydrochloride, USP (Parke-Davis), Doxorubicin Hydrochloride, USP (Adria), Heparin Sodium, USP (ESI), Hydrocortisone Sodium Phosphate (MS&D), Lidocaine Hydrochloride, USP (ESI), Multi-Vitamin Infusion (must be refrigerated-USV), Vitamin B Complex with Ascorbic Acid (Roche).

Physically Compatible Up to 24 Hours (Do not use if precipitation occurs)

Clindamycin Phosphate, USP (Upjohn), Cyclophosphamide, USP (Mead-Johnson), Insulin, USP (Lilly).

Conditionally Compatible (Use within one hour after mixing or may be infused directly into the same running IV line)

Ampicillin Sodium, USP (Bristol), Cisplatin (Bristol), Erythromycin Lactobionate, USP (Hospira), Methotrexate Sodium, USP (Lederle), Penicillin G Potassium, USP (Squibb), Tetracycline Hydrochloride, USP (Lederle).

Incompatible (Do Not Mix)

Cephalothin Sodium, USP (Lilly), Chloramphenicol Sodium, USP (Parke-Davis), Sodium Bicarbonate, USP (Hospira).

HOW SUPPLIED

PRESERVATIVE FREE.

Metoclopramide Injection, USP, 5 mg/mL metoclopramide base (present as the hydrochloride monohydrate) is supplied in the following:

Unit of Sale | Concentration
NDC 0409-3414-01 Tray containing 25 single-dose clear glass vials | 10 mg/2 mL (5 mg/mL)
NDC 0409-3414-11 Tray containing 25 single-dose amber glass vials | 10 mg/2 mL (5 mg/mL)

Store at 20°C to 25°C (68°F to 77°F). [See USP Controlled Room Temperature.]

Protect from light.

For clear glass vials- retain in carton until ready to use.

This product is light sensitive. Inspect before use and discard if either color or particulate is observed.

Do not store open single-dose vials for later use, as they contain no preservative. Discard unused portion.

Benadryl®is a registered trademark of Warner-Lambert Company.

Cogentin®is a registered trademark of Merck & Co., Inc.
For Medical Information about Metoclopramide Injection, please visit ‎ www.pfizermedinfo.comor ‎call ‎‎1‑800-438-1985.‎

Distributed by Hospira, Inc., Lake Forest, IL 60045 USA

LAB-1290-4.0

Revised: 09/2023

MEDICATION GUIDE

Metoclopramide (met” oh kloe’ pra mide) Injection, USP

You or your caregiver should read the Medication Guide before you start receiving metoclopramide injection and before you get another dose of metoclopramide injection. There may be new information. If you take another product that contains metoclopramide (such as metoclopramide tablets, metoclopramide orally disintegrating tablets, or metoclopramide oral solution), you should read the Medication Guide that comes with that product. Some of the information may be different. This Medication Guide does not take the place of talking to your doctor about your medical condition or your treatment.

What is the most important information I should know about metoclopramide?

Metoclopramide can cause serious side effects, including:

Abnormal muscle movementscalled tardive dyskinesia (TD). These movements happen mostly in the face muscles. You can not control these movements. They may not go away even after stopping metoclopramide. There is no treatment for TD, but symptoms may lessen or go away over time after you stop taking metoclopramide.

Your chances for getting TD go up:

- the longer you take metoclopramide and the more metoclopramide you take. You should not take metoclopramide for more than 12 weeks.
- if you are older, especially if you are a woman
- if you have diabetes

It is not possible for your doctor to know if youwill get TD if you take metoclopramide.

Call your doctor right away if you get movements you can not stop or control, such as:

- lip smacking, chewing, or puckering up your mouth
- frowning or scowling
- sticking out your tongue
- blinking and moving your eyes
- shaking of your arms and legs

See the section " What are the possible side effects of metoclopramide?" for more information about side effects.

What is metoclopramide?

Metoclopramide is a prescription medicine used to:

- relieve symptoms of slow stomach emptying in people with diabetes
- prevent nausea and vomiting that can happen with cancer chemotherapy
- prevent nausea and vomiting that may happen after surgery, if your doctor decides that you should not be treated with a stomach tube and suction
- help make it easier to insert a tube into the small intestine in both adults and children, if the tube does not pass into the stomach normally.
- to help empty stomach contents or to help barium move through your intestine, when you get an X-ray examination of the stomach or small intestine. It is not known if metoclopramide is safe and works in children except when used to help insert a tube into the small intestine.

Who should not receive metoclopramide?

Do not receive metoclopramide if you:

- have stomach or intestine problems that could get worse with metoclopramide, such as bleeding, blockage or a tear in your stomach or bowel wall
- have an adrenal gland tumor called pheochromocytoma
- are allergic to metoclopramide or anything in it. See the end of this Medication Guide for a list of ingredients in metoclopramide.
- take medicines that can cause uncontrolled movements, such as medicines for mental illness
- have seizures

What should I tell my doctor before receiving metoclopramide?

Tell your doctor about all of your medical conditions,including if you have:

- depression
- Parkinson's disease
- high blood pressure
- kidney problems. Your doctor may start with a lower dose.
- liver problems or heart failure. Metoclopramide may cause your body to hold fluids.
- diabetes. Your dose of insulin may need to be changed.
- breast cancer
- you are pregnant or plan to become pregnant. It is not known if metoclopramide will harm your unborn child.
- you are breastfeeding. Metoclopramide is passed into human milk and may harm your baby. Talk with your doctor about the best way to feed your baby if you take metoclopramide.

Tell your doctor about all the medicines you take, including prescription and non-prescription medicines, vitamins and herbal supplements.Metoclopramide and some other medicines can affect each other and may not work as well, or cause possible side effects. Do not start any new medicines while receiving metoclopramide until you talk with your doctor.

Especially tell your doctor if you take:

- another medicine that contains metoclopramide, such as metoclopramide tablets, metoclopramide orally disintegrating tablets, or metoclopramide oral solution
- a blood pressure medicine
- a medicine for depression, especially a Monoamine Oxidase Inhibitor (MAOI)
- insulin
- a medicine that can make you sleepy, such as anti-anxiety medicine, sleep medicines, and narcotics.

If you are not sure if your medicine is one listed above, ask your doctor or pharmacist. Know the medicines you take. Keep a list of them and show it to your doctor and pharmacist when you get a new medicine.

How will I receive metoclopramide?

- Metoclopramide will be given to you by intravenous (IV) infusion into your vein or by intramuscular (IM) injection into a large muscle. Where and how you receive your metoclopramide injection (IV or IM) will depend on why you are receiving it.
- Certain side effects can happen if metoclopramide is given too fast. See the section " What are the possible side effects of metoclopramide?"
- You should not take or receive metoclopramide for more than 12 weeks.

What should I avoid while receiving metoclopramide?

- Do not drink alcohol while receiving metoclopramide. Alcohol may make some side effects of metoclopramide worse, such as feeling sleepy.
- Do not drive, work with machines, or do dangerous tasks until you know how metoclopramide affects you. Metoclopramide may cause sleepiness.

What are the possible side effects of metoclopramide?

Metoclopramide can cause serious side effects, including:

- Abnormal muscle movements.See the section " What is the most important information I should know about metoclopramide?"
- Uncontrolled spasms of your face and neck muscles, or muscles of your body, arms, and legs (dystonia).These muscle spasms can cause abnormal movements and body positions. These spasms usually start within the first 2 days of treatment. These spasms happen more often in children and adults under age 30.
- Depression, thoughts about suicide, and suicide.Some people who take metoclopramide become depressed. You may have thoughts about hurting or killing yourself. Some people who take metoclopramide have ended their own lives (suicide).
- Neuroleptic Malignant Syndrome (NMS).NMS is a very rare but very serious condition that can happen with metoclopramide. NMS can cause death and must be treated in a hospital. Symptoms of NMS include: high fever, stiff muscles, problems thinking, very fast or uneven heartbeat, and increased sweating.
- Parkinsonism.Symptoms include slight shaking, body stiffness, trouble moving or keeping your balance. If you already have Parkinson's disease, your symptoms may become worse while you are receiving metoclopramide.

Call your doctor and get medical help right away if you:

- feel depressed or have thoughts about hurting or killing yourself
- have high fever, stiff muscles, problems thinking, very fast or uneven heartbeat, and increased sweating
- have muscle movements you can not stop or control
- have muscle movements that are new or unusual

Common side effects of metoclopramide include:

- feeling restless, sleepy, tired, dizzy, or exhausted
- headache
- confusion
- trouble sleeping

Infusion related side effects can happen if metoclopramide is given too fast.You may feel very anxious and restless for a short time, and then become sleepy while you are receiving a dose of metoclopramide. Tell your doctor or nurse right away if this happens.

You may have more side effects the longer you take metoclopramide and the more metoclopramide you take.

Tell your doctor about any side effects that bother you or do not go away. These are not all the possible side effects of metoclopramide.

Call your doctor for medical advice about side effects. You may report side effects to FDA at 1-800-FDA-1088.

General information about metoclopramide

Medicines are sometimes prescribed for purposes other than those listed in a Medication Guide.

This Medication Guide summarizes the most important information about metoclopramide. If you would like more information about metoclopramide, talk with your doctor. You can ask your doctor or pharmacist for information about metoclopramide that is written for healthcare professionals. For more information go to www.hospira.com or call 1-800-615-0187.

What are the ingredients in metoclopramide?

Active ingredient:metoclopramide

Inactive ingredients: sodium chloride, water, hydrochloric acid or sodium hydroxide

This Medication Guide has been approved by the U.S. Food and Drug Administration.

Distributed by Hospira, Inc., Lake Forest, IL 60045 USA

LAB-1291-2.0

Revised: 09/2023

PRINCIPAL DISPLAY PANEL - VIAL LABEL

Metoclopramide Inj., USP

10 mg/2 mL (5 mg/mL)

2 mL Single-dose vial

Rx only

For I.V. or I.M. use.

PRINCIPAL DISPLAY PANEL - OUTER PACKAGE

NDC 71872-7346-1

Metoclopramide Injection, USP
10 mg/2 mL (5 mg/mL)

1 x 2 mL Single-dose vials

Rx only